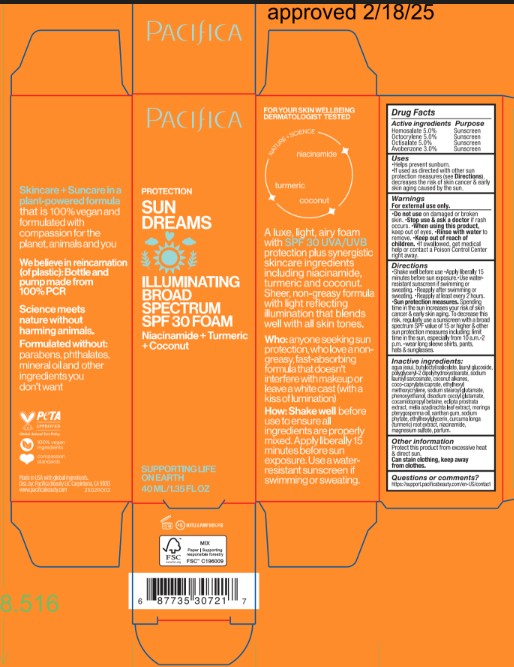 DRUG LABEL: Pacifica Sun Dreams Illuminating SPF Foam
NDC: 61197-700 | Form: AEROSOL, FOAM
Manufacturer: Pacifica Beauty, LLC
Category: otc | Type: HUMAN OTC DRUG LABEL
Date: 20250409

ACTIVE INGREDIENTS: OCTISALATE 5 mg/100 g; AVOBENZONE 3 mg/100 g; OCTOCRYLENE 5 mg/100 g; HOMOSALATE 5 mg/100 g
INACTIVE INGREDIENTS: XANTHAN GUM; SODIUM PHYTATE; NIACINAMIDE; POLYGLYCERYL-2 DIPOLYHYDROXYSTEARATE; COCO-CAPRYLATE/CAPRATE; LAURYL GLUCOSIDE; ECLIPTA PROSTRATA WHOLE; MELIA AZADIRACHTA LEAF; MORINGA PEREGRINA SEED OIL; MAGNESIUM SULFATE; BUTYLOCTYL SALICYLATE; SODIUM LAURYL SARCOSINATE; ETHYLHEXYL METHOXYCRYLENE; SODIUM STEAROYL GLUTAMATE; PHENOXYETHANOL; DISODIUM COCOYL GLUTAMATE; COCONUT ALKANES; CURCUMA LONGA (TURMERIC) ROOT; ETHYLHEXYLGLYCERIN; COCAMIDOPROPYL BETAINE; WATER

Pacifica Sun Dreams Illuminating SPF Foam

OTC Active Ingredients

Active ingredients Purpose

Homosalate 5.0% Sunscreen

Octocrylene 5.0% Sunscreen

Octisalate 5.0% Sunscreen

Avobenzone 3.0% Sunscreen

OTC Purpose

Uses

- Helps prevent sunburn.
- If used as directed with other sun protection measures (see Directions), decreases the risk of skin cancer & early skin aging caused by the sun.

Indications & Usage

Helps prevent sunburn.

Warnings

For external use only.

- Do not use on damaged or broken skin.
- Stop use & ask a doctor if rash occurs.
- When using this product, keep out of eyes.
- Rinse with water to remove.
- Keep out of reach of children.
- If swallowed, get medical help or contact a Poison Control Center right away.

Keep Out Of Reach Of Children

- Keep out of reach ofchildren.

Dosage & Administration

Directions

- Shake well before use.
- Apply liberally 15 minutes before sun exposure.
- Use water-resistant sunscreen if swimming or sweating.
- Reapply after swimming or sweating.
- Reapply at least every 2 hours.
- Sun protection measures.
- Spending time in the sun increases your risk of skin cancer & early skin aging. To decrease this risk, regularly use a sunscreen with a broad spectrum SPF value of 15 or higher & other sun protection measures including: limit time in the sun, especially from 10 a.m.-2 p.m.-wear long sleeve shirts, pants, hats & sunglasses.

Inactive ingredients

agua (eau), butyloctyl salicylate, lauryl glucoside, polyglyceryl-2 dipolyhydroxystearate, sodium lauroyl sarcosinate, coconut alkanes, coco-caprylate/caprate, ethylhexyl methoxycrylene, sodium stearoyl glutamate, phenoxywethanol, disodium cocoyl glutamate, cocamidopropyl betaine, eclipta prostrata extract, melia azadirachta leaf extract, moringa pterygosperma oil, xanthan gum, sodium phytate, ethylhexylglycerin, curcuma longa (turmeric) root extract, niacinamide, magnesium sulfate, parfum.

Other information. Protect this product from excessive heat & direct sun. Can stain clothing, keep away from clothes.

Questions or comments?

https://support.pacificabeauty.com/en-US/contact